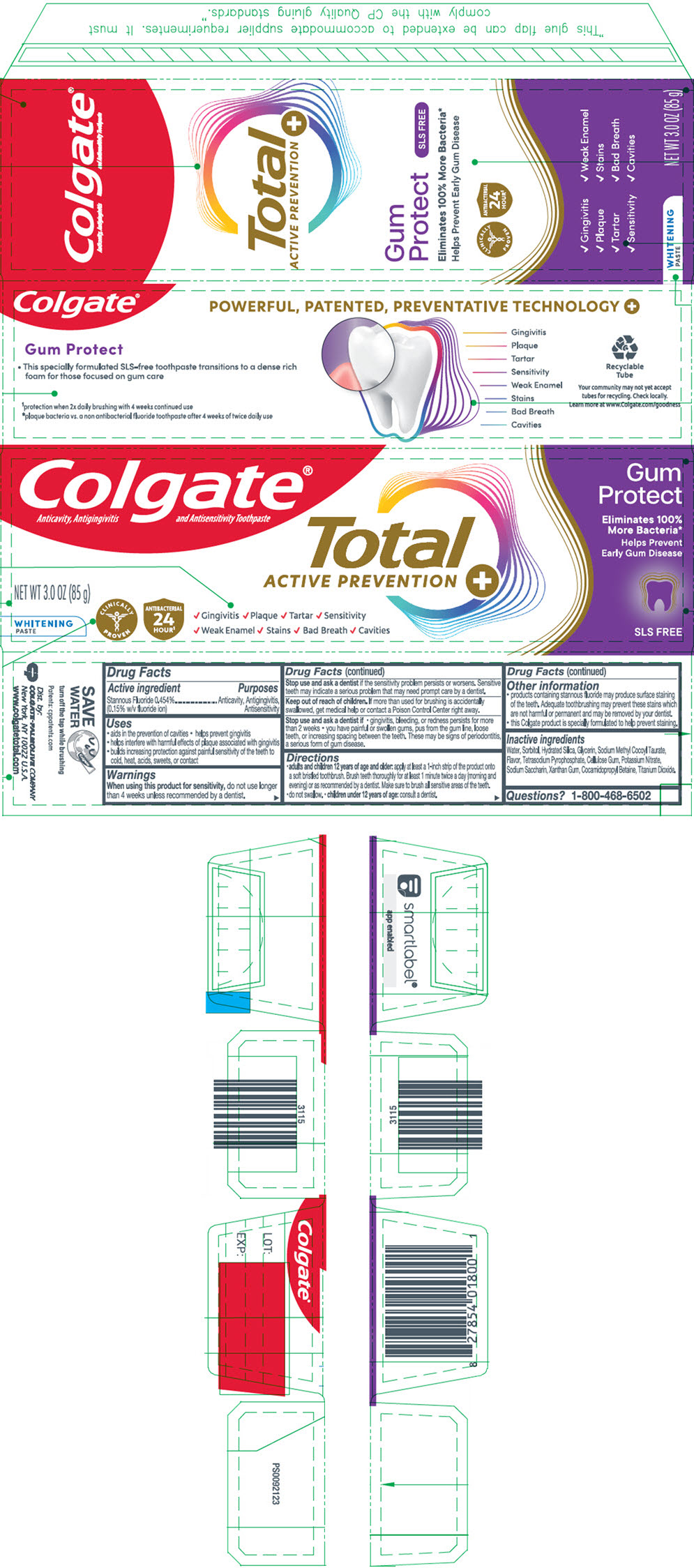 DRUG LABEL: Colgate Total Gum Protect Whitening
NDC: 35000-277 | Form: PASTE, DENTIFRICE
Manufacturer: Colgate-Palmolive Company
Category: otc | Type: HUMAN OTC DRUG LABEL
Date: 20260120

ACTIVE INGREDIENTS: STANNOUS FLUORIDE 1.1 mg/1 g
INACTIVE INGREDIENTS: WATER; SORBITOL; HYDRATED SILICA; GLYCERIN; SODIUM METHYL COCOYL TAURATE; SODIUM PYROPHOSPHATE; CARBOXYMETHYLCELLULOSE SODIUM, UNSPECIFIED; POTASSIUM NITRATE; SACCHARIN SODIUM; XANTHAN GUM; COCAMIDOPROPYL BETAINE; TITANIUM DIOXIDE

Colgate® Total Gum Protect Whitening

Drug Facts

Active ingredient

Stannous Fluoride 0.454% (0.15% w/v fluoride ion)

Purposes

Anticavity, Antigingivitis, Antisensitivity

Uses

- aids in the prevention of cavities
- helps prevent gingivitis
- helps interfere with harmful effects of plaque associated with gingivitis
- builds increasing protection against painful sensitivity of the teeth to cold, heat, acids, sweets, or contact

Warnings

When using this product for sensitivity, do not use longer than 4 weeks unless recommended by a dentist.

Stop use and ask a dentist if the sensitivity problem persists or worsens. Sensitive teeth may indicate a serious problem that may need prompt care by a dentist.

Keep out of reach of children. If more than used for brushing is accidentally swallowed, get medical help or contact a Poison Control Center right away.

Stop use and ask a dentist if

- gingivitis, bleeding, or redness persists for more than 2 weeks
- you have painful or swollen gums, pus from the gum line, loose teeth, or increasing spacing between the teeth. These may be signs of periodontitis, a serious form of gum disease.

Directions

- adults and children 12 years of age and older: apply at least a 1-inch strip of the product onto a soft bristled toothbrush. Brush teeth thoroughly for at least 1 minute twice a day (morning and evening) or as recommended by a dentist. Make sure to brush all sensitive areas of the teeth.
- do not swallow.
- children under 12 years of age: consult a dentist.

Other information

- products containing stannous fluoride may produce surface staining of the teeth. Adequate toothbrushing may prevent these stains which are not harmful or permanent and may be removed by your dentist.
- this Colgate product is specially formulated to help prevent staining.

Inactive ingredients

Water, Sorbitol, Hydrated Silica, Glycerin, Sodium Methyl Cocoyl Taurate, Flavor, Tetrasodium Pyrophosphate, Cellulose Gum, Potassium Nitrate, Sodium Saccharin, Xanthan Gum, Cocamidopropyl Betaine, Titanium Dioxide.

Questions?

1-800-468-6502

Dist. by:
COLGATE-PALMOLIVE COMPANY
New York, NY 10022 U.S.A.

PRINCIPAL DISPLAY PANEL - 85 g Tube Carton

Colgate®
Anticavity, Antigingivitis and Antisensitivity Toothpaste

Total
ACTIVE PREVENTION +

Gum
Protect

Eliminates 100%
More Bacteria*

Helps Prevent
Early Gum Disease

NET WT 3.0 OZ (85 g)

WHITENING
PASTE

CLINICALLY
PROVEN

ANTIBACTERIAL
24
HOUR^1

✓ Gingivitis ✓ Plaque ✓ Tartar ✓ Sensitivity
✓ Weak Enamel ✓ Stains ✓ Bad Breath ✓ Cavities

SLS FREE